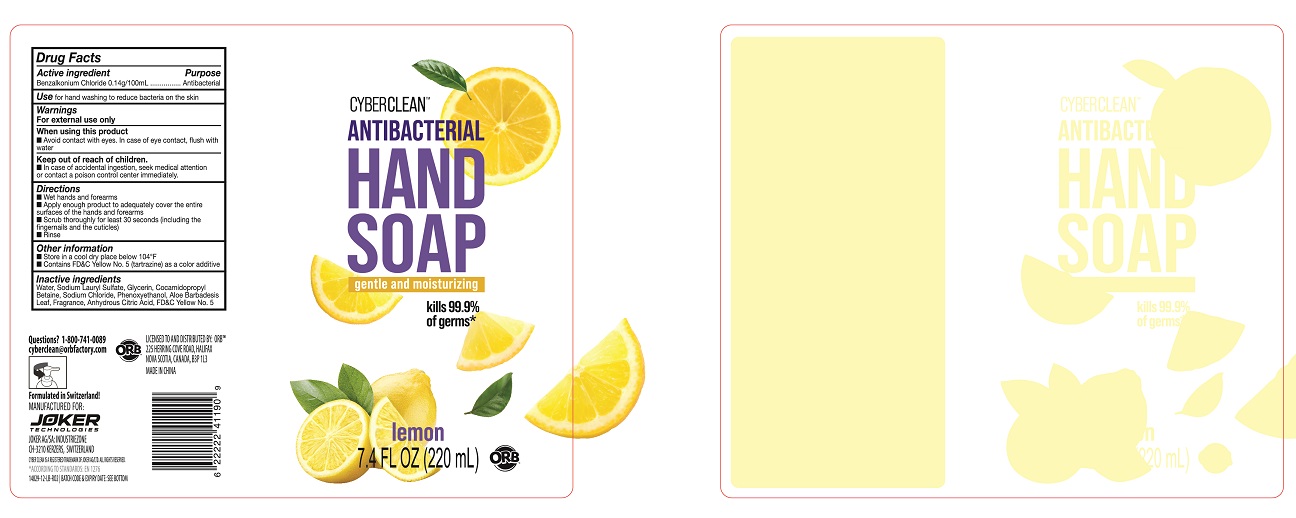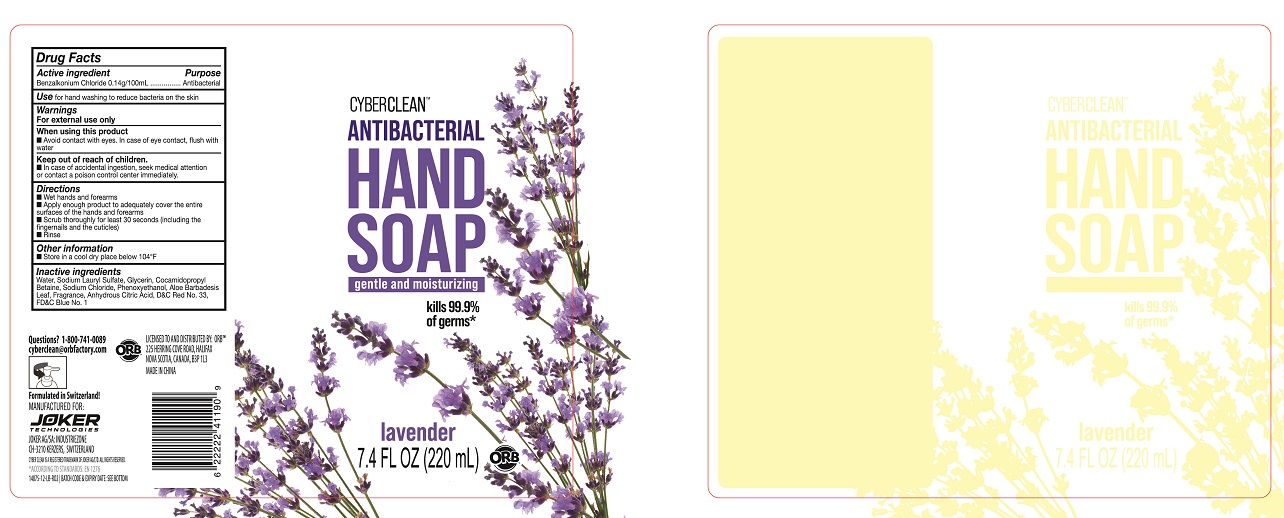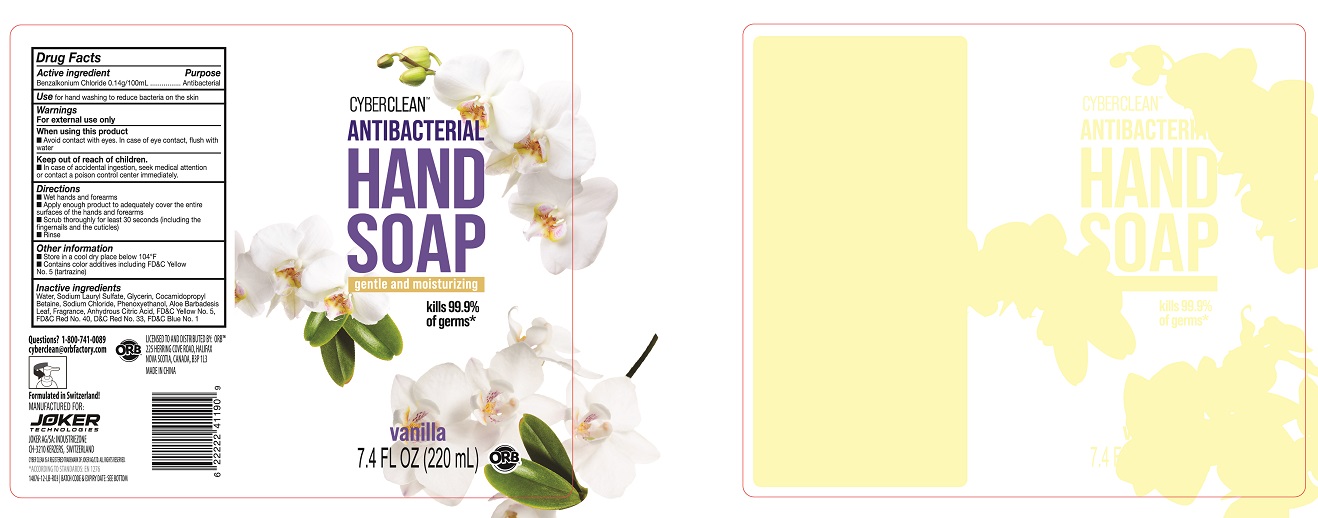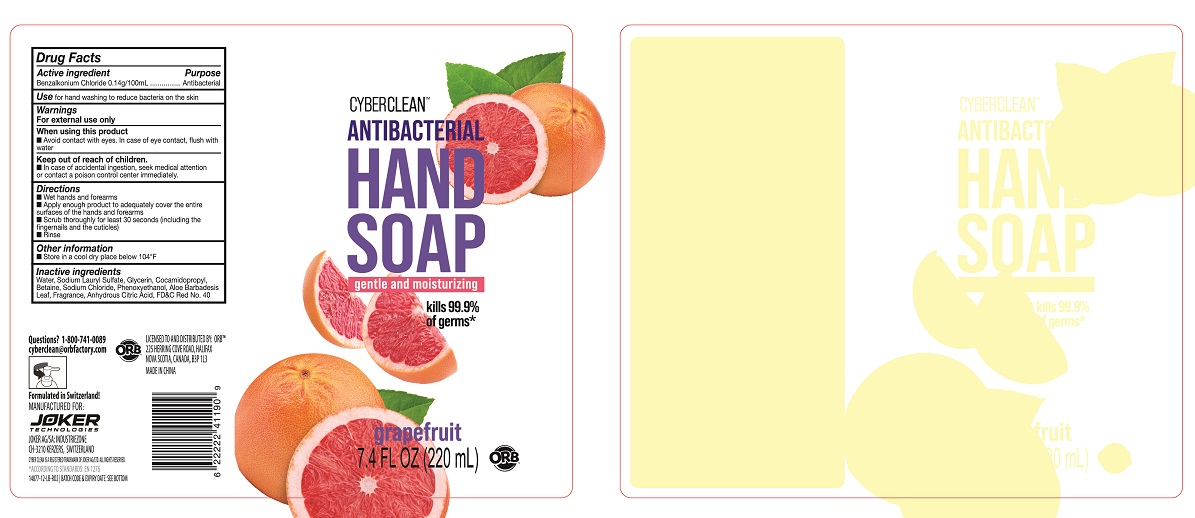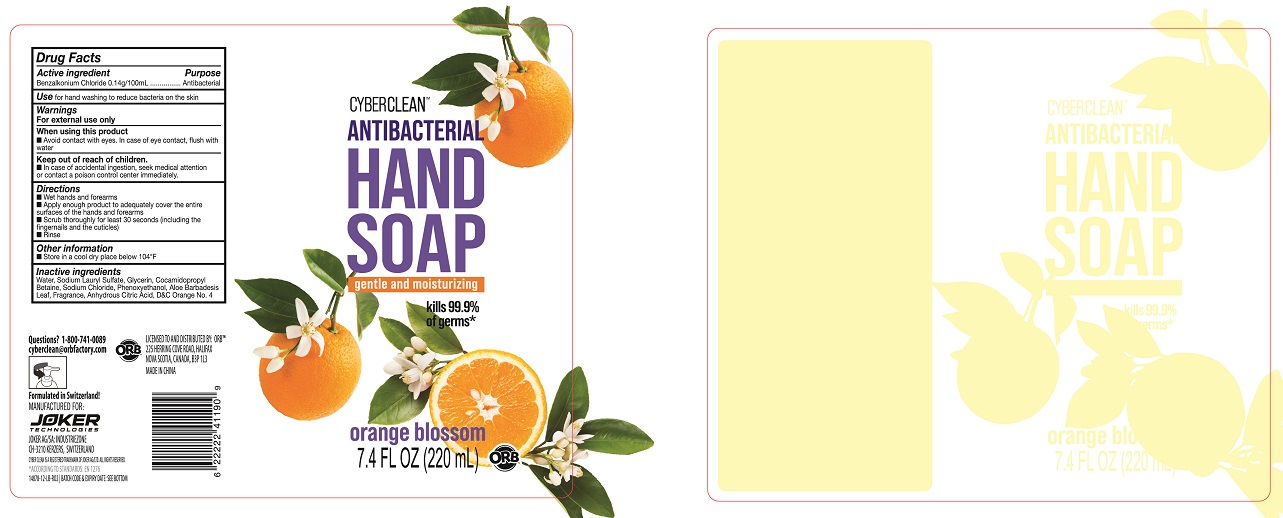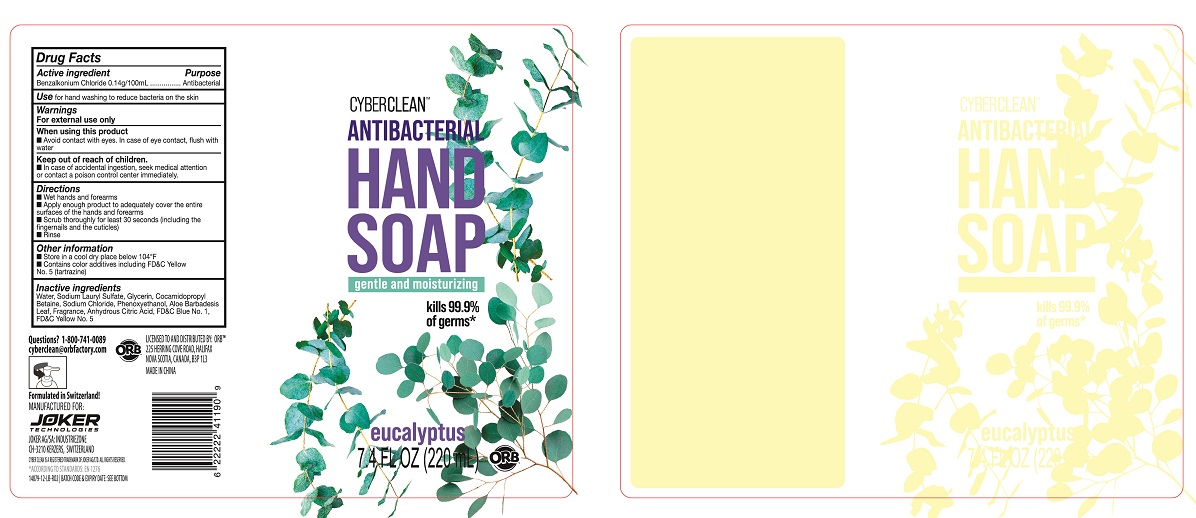 DRUG LABEL: Cyber Clean Antibacterial HandSoap Eucalyptus
NDC: 75757-120 | Form: LIQUID
Manufacturer: JOKER AG
Category: otc | Type: HUMAN OTC DRUG LABEL
Date: 20210126

ACTIVE INGREDIENTS: BENZALKONIUM CHLORIDE 0.14 g/100 mL
INACTIVE INGREDIENTS: FD&C YELLOW NO. 5; FD&C BLUE NO. 1; PHENOXYETHANOL; SODIUM CHLORIDE; ALOE VERA LEAF; GLYCERIN; SODIUM LAURYL SULFATE; WATER; COCAMIDOPROPYL BETAINE; ANHYDROUS CITRIC ACID

Cyber Clean Antibacterial Hand Soap Lemon
Cyber Clean Antibacterial Hand Soap Grapefruit
Cyber Clean Antibacterial Hand Soap Vanilla
Cyber Clean Antibacterial Hand Soap Eucalyptus
Cyber Clean Antibacterial Hand Soap Orange Blossom
Cyber Clean Antibacterial Hand Soap Lavender

Cyber Clean Antibacterial Hand Soap Lemon
Cyber Clean Antibacterial Hand Soap Grapefruit
Cyber Clean Antibacterial Hand Soap Vanilla
Cyber Clean Antibacterial Hand Soap Eucalyptus
Cyber Clean Antibacterial Hand Soap Orange Blossom
Cyber Clean Antibacterial Hand Soap Lavender

Active Ingredient(s)

Benzalkonium chloride 0.14g/100mL. Purpose: Antiseptic

Purpose

Antiseptic

Use

Cyber Clean Antibacterial Hand Soap to help reduce bacteria that potentially can cause disease.

Warnings

For external use only.

Do not use

- in children less than 2 months of age
- on open skin wounds

When using this product keep out of eyes, ears, and mouth. In case of contact with eyes, rinse eyes thoroughly with water.
Stop use and ask a doctor if irritation or rash occurs. These may be signs of a serious condition.
Keep out of reach of children. If swallowed, get medical help or contact a Poison Control Center right away.

Stop use and ask a doctor if irritation or rash occurs. These may be signs of a serious condition.

Keep out of reach of children. If swallowed, get medical help or contact a Poison Control Center right away.

Directions

- Wet hands and forearms
- Apply enough product to adequately cover the entire surfaces of the hands and forearms
- Scrub thoroughly for least 30 seconds(including the fingernails and the cuticles)
- Rinse

Other information

- Store between 15-30C (59-86F)
- Avoid freezing and excessive heat above 40C (104F)

Inactive ingredients

Cyber Clean Antibacterial Hand Soap Lemon:

Water
Sodium dodecyl sulfate
Sodium chloride
Cocamidopropyl betaine
Glycerin
Phenoxyethanol
Aloe Vera Extract
Citric Acid anhydrous
FD&C Yellow 5 (Tartrazine)

Cyber Clean Antibacterial Hand Soap Grapefruit:

Water
Sodium dodecyl sulfate
Sodium chloride
Cocamidopropyl betaine
Glycerin
Phenoxyethanol
Aloe Vera Extract
Citric Acid anhydrous
FD&C Red 40

Cyber Clean Antibacterial Hand Soap Vanilla:

Water
Sodium dodecyl sulfate
Sodium chloride
Cocamidopropyl betaine
Glycerin
Phenoxyethanol
Aloe Vera Extract
Citric Acid anhydrous
D&C Red 33
FD&C Red 40
FD&C Blue 1

Cyber Clean Antibacterial Hand Soap Eucalyptus:

Water
Sodium dodecyl sulfate
Sodium chloride
Cocamidopropyl betaine
Glycerin
Phenoxyethanol
Aloe Vera Extract
Citric Acid anhydrous
FD&C Yellow 5 (Tartrazine)
FD&C Blue 1

Cyber Clean Antibacterial Hand Soap Orange Blossom:

Water
Sodium dodecyl sulfate
Sodium chloride
Cocamidopropyl betaine
Glycerin
Phenoxyethanol
Aloe Vera Extract
Citric Acid anhydrous
D&C Orange 4

Cyber Clean Antibacterial Hand Soap Lavender:

Water
Sodium dodecyl sulfate
Sodium chloride
Cocamidopropyl betaine
Glycerin
Phenoxyethanol
Aloe Vera Extract
Citric Acid anhydrous
D&C Red 33
FD&C Blue 1